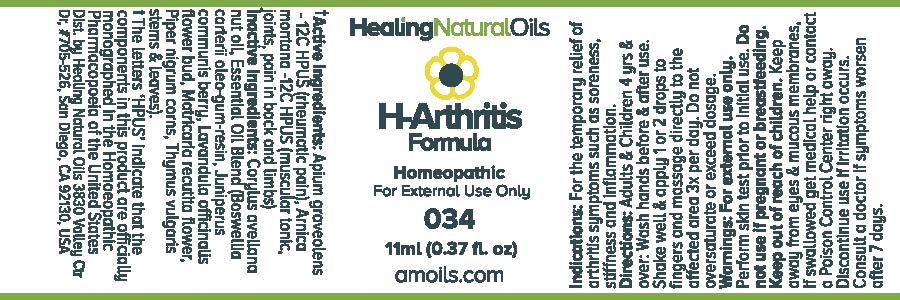 DRUG LABEL: H-Arthritis Formula
                
                        
NDC: 61077-034 | Form: OIL
Manufacturer: Healing Natural Oils LLC
Category: homeopathic | Type: HUMAN OTC DRUG LABEL
Date: 20171227

ACTIVE INGREDIENTS: CELERY SEED 12 [hp_C]/11 mL; ARNICA MONTANA 12 [hp_C]/11 mL
INACTIVE INGREDIENTS: EUROPEAN HAZELNUT OIL; FRANKINCENSE OIL; JUNIPER BERRY; LAVANDULA ANGUSTIFOLIA FLOWER; CHAMOMILE; WHITE PEPPER OIL; THYME

Active Ingredients:

Apium graveolens - 12C HPUS,
Arnica montana - 12C HPUS

Purpose

Apium graveolens - 12C HPUS (rheumatic pain),
Arnica montana -12C HPUS (muscular tonic, joints, pain in back and limbs)

The letters ‘HPUS’ indicate that the components in this product are officially
monographed in the Homoeopathic Pharmacopoeia of the United States

Inactive Ingredients:

Corylus avellana nut oil, Essential Oil Blend (Boswellia carteri
oleo-gum-resin, Juniperus communis berry,
Lavandula officinalis flower bud, Matricaria
recutita flower, Piper nigrum corns, Thymus
vulgaris stems and leaves)

Indications:

For the temporary relief of arthritis symptoms such as soreness, stiffness and inflammation.

Directions:

Adults and Children 4 yrs and over: Wash hands before and after use.
Shake well and apply 1 or 2 drops to fingers and massage directly to the affected area 3x per day.
Do not oversaturate or exceed dosage.

Warnings:

For external use only.
Perform skin test prior to initial use.

Do not use if pregnant or breastfeeding.

Keep out of reach of children.

OTHER SAFETY INFORMATION

Keep away from eyes and mucous membranes. If swallowed get medical help or contact a Poison Control
Center right away.

Discontinue use if irritation occurs.

ASK DOCTOR

Consult a doctor if symptoms worsen after 7 days.

DESCRIPTION

Dist. by Healing Natural Oils 3830 Valley Ctr Dr, #705-526, San Diego, CA 92130, USA

PACKAGE LABEL

Healing Natural Oils

H-Arthritis

Formula

Homeopathic

For External Use Only

034

11ml (0.37 fl. oz)
amoils.com